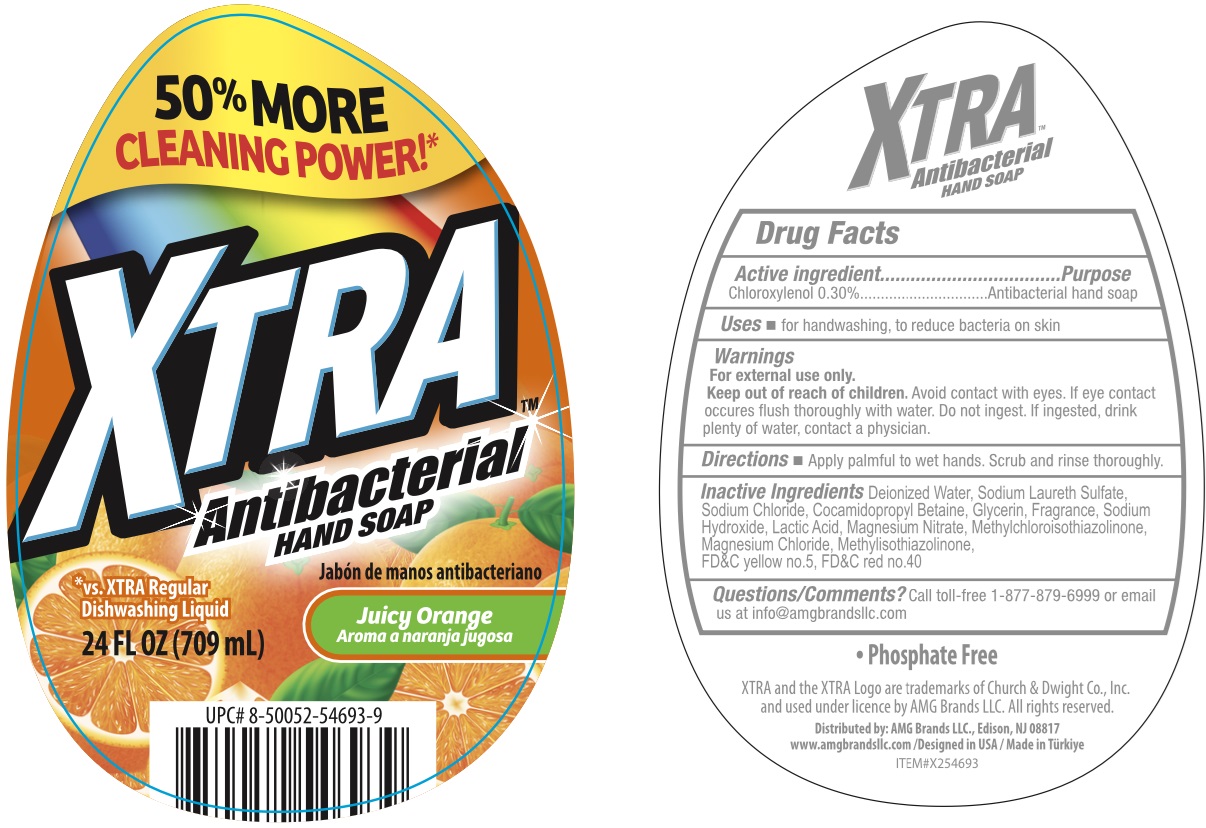 DRUG LABEL: Xtra Antibacterial Hand Juicy Orange
NDC: 51628-0033 | Form: GEL
Manufacturer: MY IMPORTS USA, LLC
Category: otc | Type: HUMAN OTC DRUG LABEL
Date: 20260223

ACTIVE INGREDIENTS: CHLOROXYLENOL 3 mg/1 mL
INACTIVE INGREDIENTS: GLYCERIN; SODIUM HYDROXIDE; LACTIC ACID, UNSPECIFIED FORM; MAGNESIUM NITRATE; METHYLCHLOROISOTHIAZOLINONE; MAGNESIUM CHLORIDE; METHYLISOTHIAZOLINONE; FD&C YELLOW NO. 5; FD&C RED NO. 40; WATER; SODIUM LAURETH-3 SULFATE; SODIUM CHLORIDE; COCAMIDOPROPYL BETAINE

Xtra Antibacterial Hand Soap Juicy Orange

Active ingredient

Chloroxylenol 0.30%

Purpose

Antibacterial hand soap

Uses

- for handwashing, to reduce bacteria on skin

Warnings

For external use only.

Keep out of reach of children.

Avoid contact with eyes. If eye contact occures flush thoroughly with water. Do not ingest. If ingested, drink plenty of water, contact a physician.

Directions

- Apply palmful to wet hands. Scrub and rinse thoroughly.

Inactive Ingredients

Deionized Water, Sodium Laureth Sulfate, Sodium Chloride, Cocamidopropyl Betaine, Glycerin, Fragrance, Sodium Hydroxide, Lactic Acid, Magnesium Nitrate, Methylchloroisothiazolinone, Magnesium Chloride, Methylisothiazolinone, FD&C yellow no.5, FD&C red no.40

Questions/Comments?

Call toll-free 1-877-879-6999 or email us at info@amgbrandsllc.com